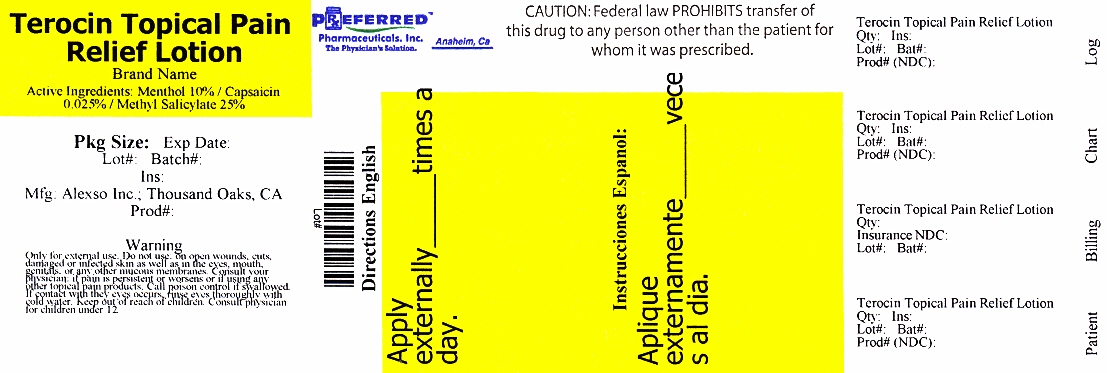 DRUG LABEL: Terocin
NDC: 68788-9496 | Form: LOTION
Manufacturer: Preferred Pharmaceuticals, Inc.
Category: otc | Type: HUMAN OTC DRUG LABEL
Date: 20140325

ACTIVE INGREDIENTS: METHYL SALICYLATE 25 g/100 mL; CAPSAICIN 0.025 g/100 mL; MENTHOL 10 g/100 mL; LIDOCAINE HYDROCHLORIDE 2.5 g/100 mL
INACTIVE INGREDIENTS: WATER; PROPYLENE GLYCOL; CETYL ALCOHOL; STEARIC ACID; GLYCERYL MONOSTEARATE; PEG-100 STEARATE; DIMETHYL SULFONE; ALOE VERA LEAF; BORAGE OIL; INDIAN FRANKINCENSE; XANTHAN GUM; TROLAMINE; METHYLPARABEN; PROPYLPARABEN; DMDM HYDANTOIN; IODOPROPYNYL BUTYLCARBAMATE

Terocin Topical Pain Relief Lotion

Active ingredient

Methyl Salicylate 25%

Capsaicin 0.025%

Menthol 10%

Lidocaine 2.50%

Purpose

Topical Analgesic

Uses

Temporarily relieves mild aches and pains of muscles or joints.

Warnings

- Only for external use.
- Do not use: on open wounds, cuts, damaged or infected skin as well as in the eyes, mouth, genitals, or any other mucous membranes.
- Consult your physician: if pain is persistent or worsens or if using any other topical pain products.
- Call poison control if swallowed. If contact with the eyes occurs, rinse eyes thoroughly with cold water.

Keep out of reach of children.

Consult physician for children under 12.

Directions

Wash and dry affected area. Shake bottle well before each use and gently rub

over area of pain. Use is not recommended more than four times a day. Wash

hands immediately afterwards to avoid contact with eyes.

Inactive ingredients

Water (Aqua), Propylene Glycol, Cetyl Alcohol, Stearic Acid, Glyceryl Stearate,

PEG-100 Stearate, Dimethyl Sulfone, Aloe Barbadensis Leaf Extract, Borago

Officinalis Seed Oil, Boswellia Serrata Extract, Xanthan Gum, Triethanolamine,

Methylparaben, Propylparaben, DMDM Hydantoin, Iodopropynyl Butylcarbamate.

Package/Label Principal Display Panel

NDC 68788-9496-1

Terocin (terodoloricin) Topical Pain Relief Lotion

Long Lasting

Soothing Effect

120 ml (4 fl oz.)

Manufactured for: Alexso Inc.

Thousand Oaks, CA 91360

Made in U.S.A.

Patent Pending

Package Label